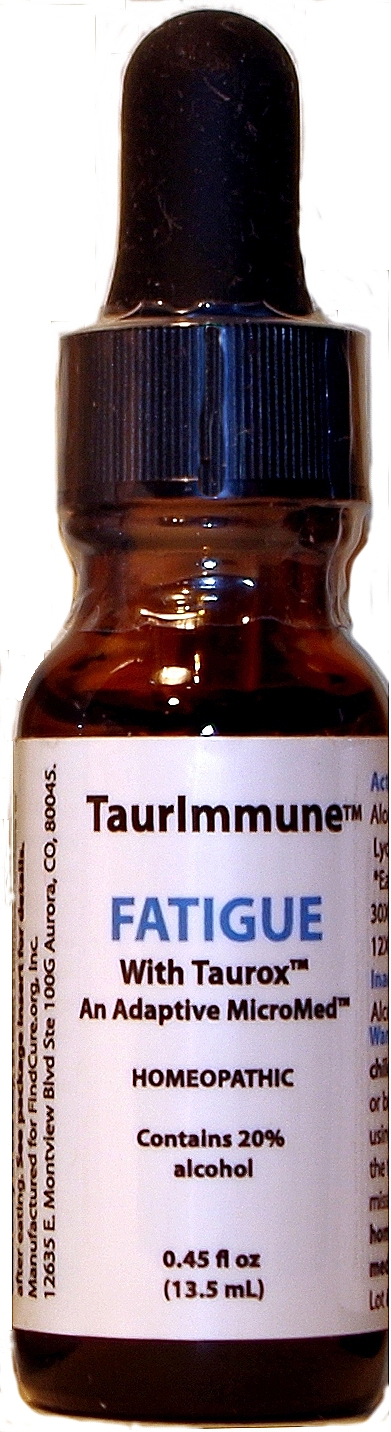 DRUG LABEL: TaurImmune Fatigue
NDC: 73311-123 | Form: LIQUID
Manufacturer: CureImmune Corp
Category: homeopathic | Type: HUMAN OTC DRUG LABEL
Date: 20190906

ACTIVE INGREDIENTS: ARNICA MONTANA 6 [hp_X]/1 1; ALOE 6 [hp_X]/1 1; PICEA MARIANA RESIN 6 [hp_X]/1 1; LYCOPODIUM CLAVATUM SPORE 6 [hp_X]/1 1; SELENICEREUS GRANDIFLORUS STEM 6 [hp_X]/1 1; OYSTER SHELL CALCIUM CARBONATE, CRUDE 8 [hp_X]/1 1; ZINC CARBOBENZOXY-.BETA.-ALANYLTAURINATE 6 [hp_X]/1 1
INACTIVE INGREDIENTS: WATER; ALCOHOL

Taurimmune fatigue drops

Active Ingredients

Abies nig.*, Aloe*, Arnica*, Cactus*,
Lycopodium*, Tauroxicum* (COBAT).
*Each at 6X(14%), 12X (0.14%),
30X(0.14%).

Calc. carb. 10X(14%),
12X(0.15%), 30X (0.14%).

Use

Immune support and treatment of fatigue. May also help treat or prevent allergies and cold & flu symptoms.

PURPOSE

For treatment of moderate to severe fatigue due to illness or other conditions. Immune support. May also help treat symptoms of colds, flu and allergies.

Directions

Directions for adults and children 15 years of age and older: Place 10 drops under tongue once daily, or as directed by a health professional. Hold in mouth 30 seconds. Best if taken early in the day, at least 5 minutes before or after eating. See package insert for details.

Warnings

Keep out of reach of children. Do not use if you are pregnant or breast feeding, an organ recipient, using immunosuppressive drugs, or if the tamper-evident seal is broken or missing. See package insert for details.

Keep out of reach of children.

Inactive Ingredients

20% alcohol (ethanol), purified water

Disclaimer

Claims based on traditional
homeopathic practice, not accepted
medical evidence. Not FDA evaluated.

PACKAGE LABEL

TaurImmune

FATIGUE

With Taurox
An Adaptive MicroMed
HOMEOPATHIC
Contains 20 percent alcohol
0.45 oz
13.5 mL

productfatig3.jpg